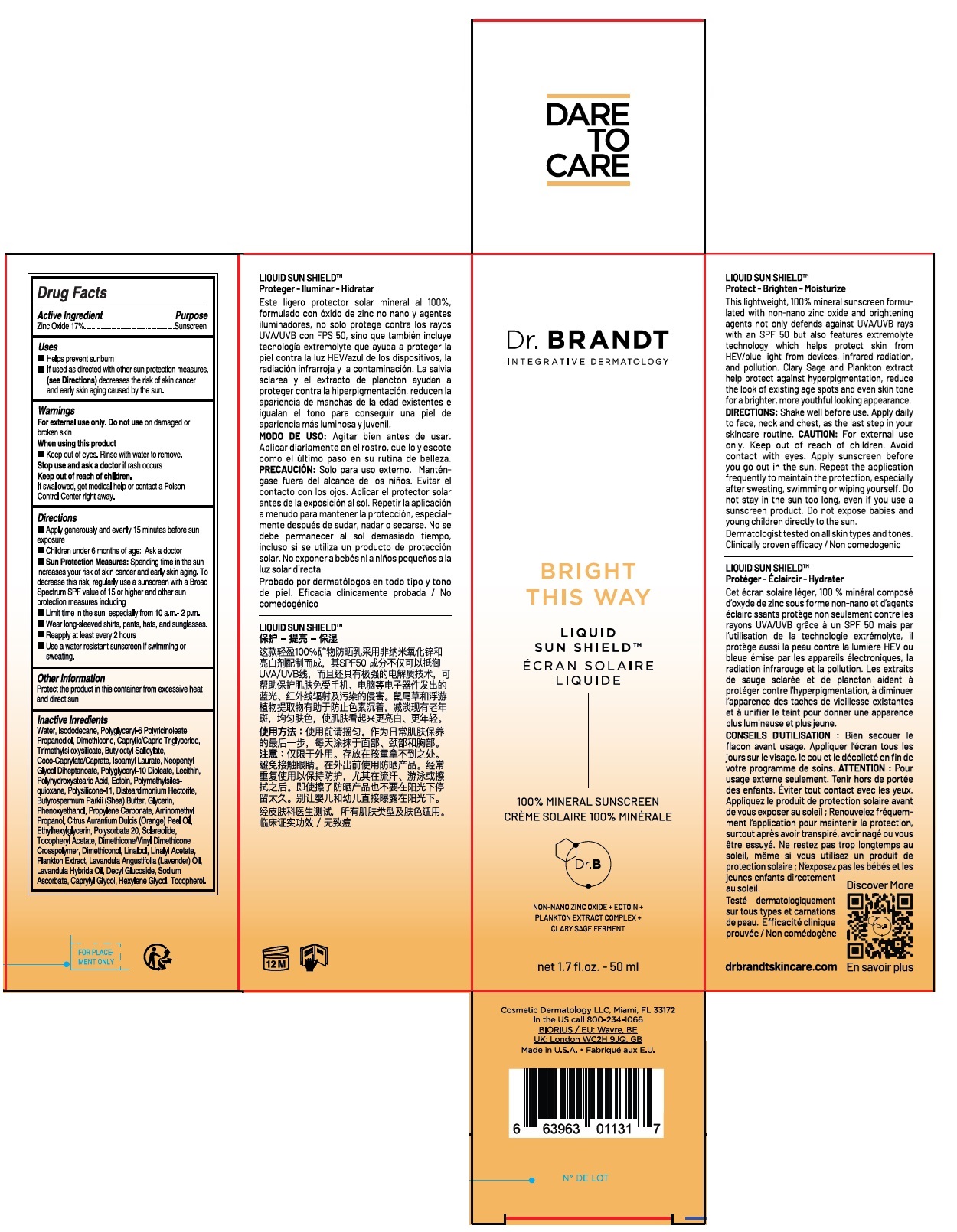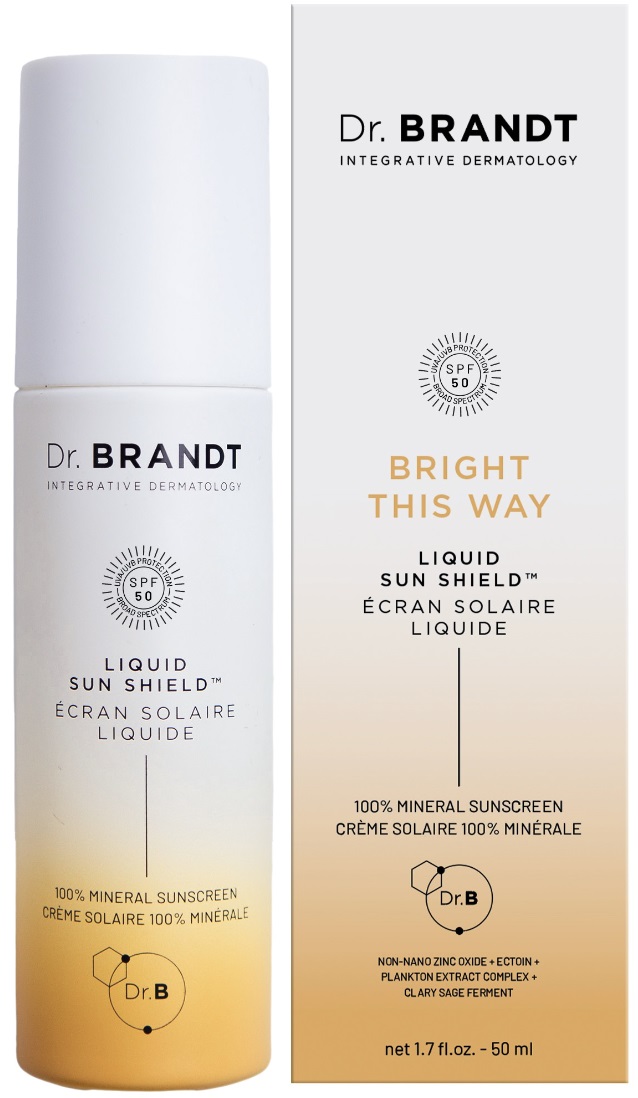 DRUG LABEL: dr. brandt SUN SHIELD SPF 50
NDC: 81568-101 | Form: LIQUID
Manufacturer: Dr. Brandt
Category: otc | Type: HUMAN OTC DRUG LABEL
Date: 20240828

ACTIVE INGREDIENTS: ZINC OXIDE 17 g/100 mL
INACTIVE INGREDIENTS: WATER; ISODODECANE; POLYGLYCERYL-6 POLYRICINOLEATE; PROPANEDIOL; DIMETHICONE, UNSPECIFIED; MEDIUM-CHAIN TRIGLYCERIDES; TRIMETHYLSILOXYSILICATE (M/Q 0.6-0.8); BUTYLOCTYL SALICYLATE; COCOYL CAPRYLOCAPRATE; ISOAMYL LAURATE; NEOPENTYL GLYCOL DIHEPTANOATE; POLYGLYCERYL-10 DIOLEATE; SOYBEAN LECITHIN; POLYHYDROXYSTEARIC ACID (2300 MW); ECTOINE; POLYMETHYLSILSESQUIOXANE (4.5 MICRONS); DISTEARDIMONIUM HECTORITE; SHEA BUTTER; GLYCERIN; PHENOXYETHANOL; PROPYLENE CARBONATE; AMINOMETHYLPROPANOL; ORANGE OIL, COLD PRESSED; ETHYLHEXYLGLYCERIN; POLYSORBATE 20; SCLAREOLIDE; .ALPHA.-TOCOPHEROL ACETATE; DIMETHICONE/VINYL DIMETHICONE CROSSPOLYMER (SOFT PARTICLE); DIMETHICONOL (600000 CST); LINALOOL, (+/-)-; LINALYL ACETATE; CHLORELLA VULGARIS; LAVENDER OIL; LAVANDIN OIL; DECYL GLUCOSIDE; SODIUM ASCORBATE; CAPRYLYL GLYCOL; HEXYLENE GLYCOL; TOCOPHEROL

Dr. BRANDT LIQUID SUN SHIELDTM

Active Ingredient

Zinc Oxide 17%

Purpose

Sunscreen

Uses

• Helps prevent sunburn
• If used as directed with other sun protection measures, (See Directions) decreases the risk of skin cancer and early skin aging caused by the sun.

Warnings

For external use only. Do not use on damaged or broken skin

When using this product
• Keep out of eyes. Rinse with water to remove.

Stop use and ask a doctor if rash occurs

Keep out of reach of children.
If swallowed, get medical help or contact a Poison Control Center right away.

Directions

• Apply generously and evenly 15 minutes before sun exposure
• Children under 6 months of age: Ask a doctor
• Sun Protection Measures: Spending time in the sun increases your risk of skin cancer and early skin aging. To decrease this risk, regularly use a sunscreen with a Broad Spectrum SPF value of 15 or higher and other sun protection measures including
• Limit time in the sun, especially from 10 a.m.-2 p.m.
• Wear long-sleeved shirts, pants, hats and sunglasses.
• Reapply at least every 2 hours
• Use a water resistant sunscreen if swimming or sweating.

Other Information

Protect the product in this container from excessive heat and direct sun

Inactive Ingredients

Water, Isododecane, Polyglyceryl-6 Polyricinoleate, Propanediol, Dimethicone, Caprylic/Capric Triglyceride, Trimethylsiloxysilicate, Butyloctyl Salicylate, Coco-Caprylate/Caprate, Isoamyl Laurate, Neopentyl Glycol Diheptanoate, Polyglyceryl-10 Dioleate, Lecithin, Polyhydroxystearic Acid, Ectoin, Polymethylsilsesquioxane, Polysilicone-11, Disteardimonium Hectorite, Butyrospermum Parkii (Shea) Butter, Glycerin, Phenoxyethanol, Propylene Carbonate, Aminomethyl Propanol, Citrus Aurantium Dulcis (Orange) Peel Oil, Ethylhexylglycerin, Polysorbate 20, Sclareolide, Tocopheryl Acetate, Dimethicone/Vinyl Dimethicone Crosspolymer, Dimethiconol, Linalool, Linalyl Acetate, Plankton Extract, Lavandula Angustifolia (Lavender) Oil, Lavandula Hybrida Oil, Decyl Glucoside, Sodium Ascorbate, Caprylyl Glycol, Hexylene Glycol, Tocopherol.

INTEGRATIVE DERMATOLOGY

SPF 50 UVA/UVB PROTECTION BROAD SPECTRUM

BRIGHT THIS WAY

100% MINERAL SUNSCREEN

NON-NANO ZINC OXIDE + ECTOIN + PLANKTON EXTRACT COMPLEX + CLARY SAGE FERMENT

LIQUID SUN SHIELDTM
Protect - Brighten - Moisturize

This lightweight, 100% mineral sunscreen formulated with non-nano zinc oxide and brightening agents not only defends against UVA/UVB rays with an SPF 50 but also features extremolyte technology which helps protect skin from HEV/blue light from devices, infrared radiation, and pollution. Clary Sage and Plankton extract help protect against hyperpigmentation, reduce the look of existing age spots and even skin tone for a brighter, more youthful looking appearance.

DIRECTIONS: Shake well before use. Apply daily to face, neck and chest, as the last step in your skincare routine. CAUTION: For external use only. Keep out of reach of children. Avoid contact with eyes. Apply sunscreen before you go out in the sun. Repeat the application frequently to maintain the protection, especially after sweating, swimming or wiping yourself. Do not stay in the sun too long, even if you use a sunscreen product. Do not expose babies and young children directly to the sun.

Dermatologist tested on all skin types and tones. Clinically proven efficacy / Non comedogenic

drbrandtskincare.com

DARE TO CARE

Cosmetic Dermatology LLC, Miami, FL 33172
In the US call 800-234-1066
BIORIUS / EU: Wavre, BE
UK: London WC2H 9JQ, GB
Made in U.S.A.